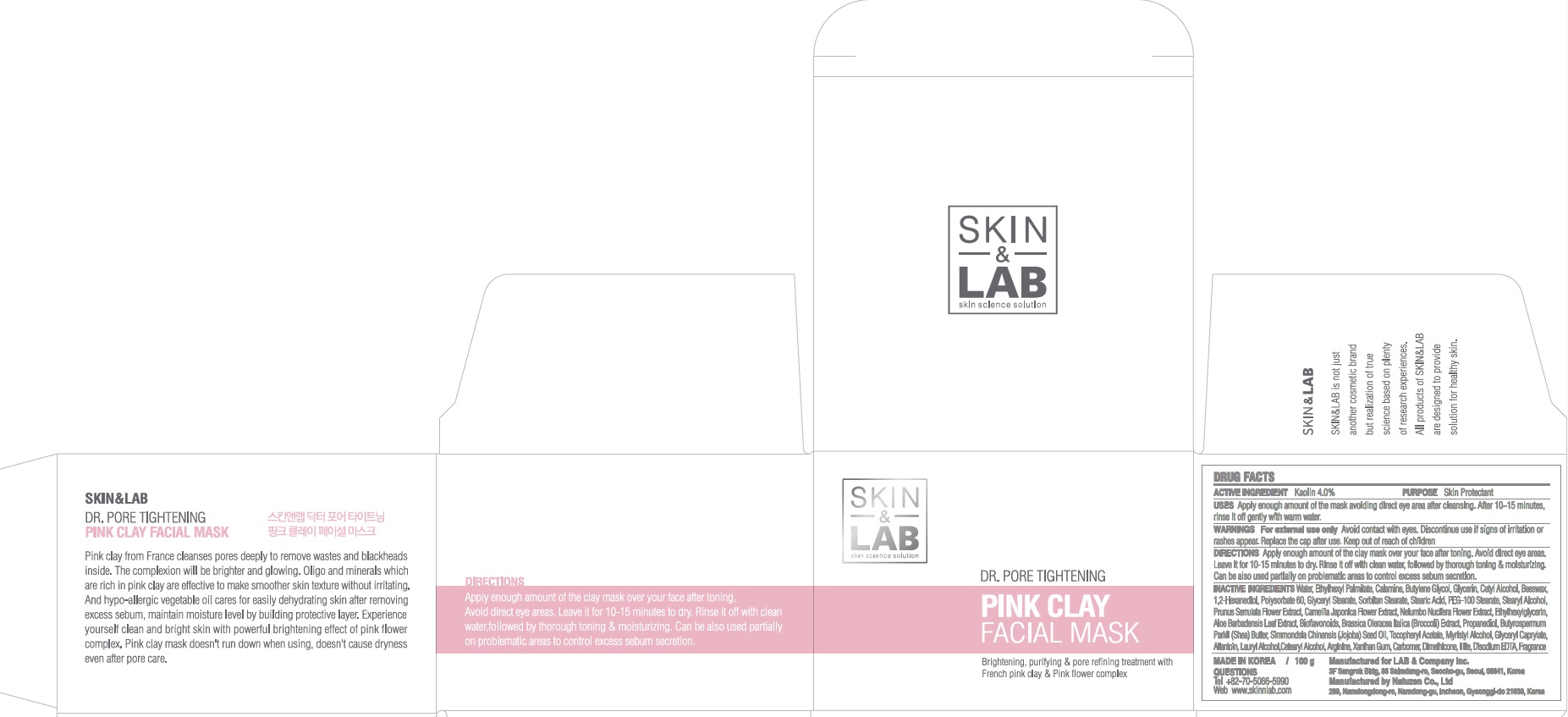 DRUG LABEL: Dr Pore Tightening PINK CLAY FACIAL MASK
NDC: 69457-060 | Form: CREAM
Manufacturer: LAB & Company Inc.
Category: otc | Type: HUMAN OTC DRUG LABEL
Date: 20171207

ACTIVE INGREDIENTS: Kaolin 4.0 g/100 g
INACTIVE INGREDIENTS: Water; Glycerin

ACTIVE INGREDIENT

Active ingredients: Kaolin 4.0%

INACTIVE INGREDIENT

Inactive ingredients: Water, Ethylhexyl Palmitate, Calamine, Butylene Glycol, Glycerin, Cetyl Alcohol, Beeswax, 1,2-Hexanediol, Polysorbate 60, Glyceryl Stearate, Sorbitan Stearate, Stearic Acid, PEG-100 Stearate, Stearyl Alcohol, Prunus Serrulata Flower Extract, Camellia Japonica Flower Extract, Nelumbo Nucifera Flower Extract, Ethylhexylglycerin, Aloe Barbadensis Leaf Extract, Bioflavonoids, Brassica Oleracea Italica (Broccoli) Extract, Propanediol, Butyrospermum Parkii (Shea) Butter, Simmondsia Chinensis (Jojoba) Seed Oil, Tocopheryl Acetate, Myristyl Alcohol, Glyceryl Caprylate, Allantoin, Lauryl Alcohol, Cetearyl Alcohol, Arginine, Xanthan Gum, Carbomer, Dimethicone, Illite, Disodium EDTA, Fragrance

PURPOSE

Purpose: Skin Protectant

WARNINGS

Warnings: For external use only. Avoid contact with eyes. Discontinue use if signs of irritation or rashes appear. Replace the cap after use. Keep out of reach of children.

Keep out of reach of children: Keep out of reach of babies and children.

QUESTIONS

Tel: +82-70-5066-5990

Web: www.skinnlab.com

Uses

Uses: Apply enough amount of the mask avoiding direct eye area after cleasning. After 10~15 minutes, rinse it off gently with warm water

Directions

Directions: Apply enough amount of the clay mask over your face after toning. Avoid direct eye areas. Leave it for 10-15 minutes to dry. Rinse it off with clean water, followed by thorough toning & moisturizing. Can be also used partially on problematic areas to control excess sebum secretion.